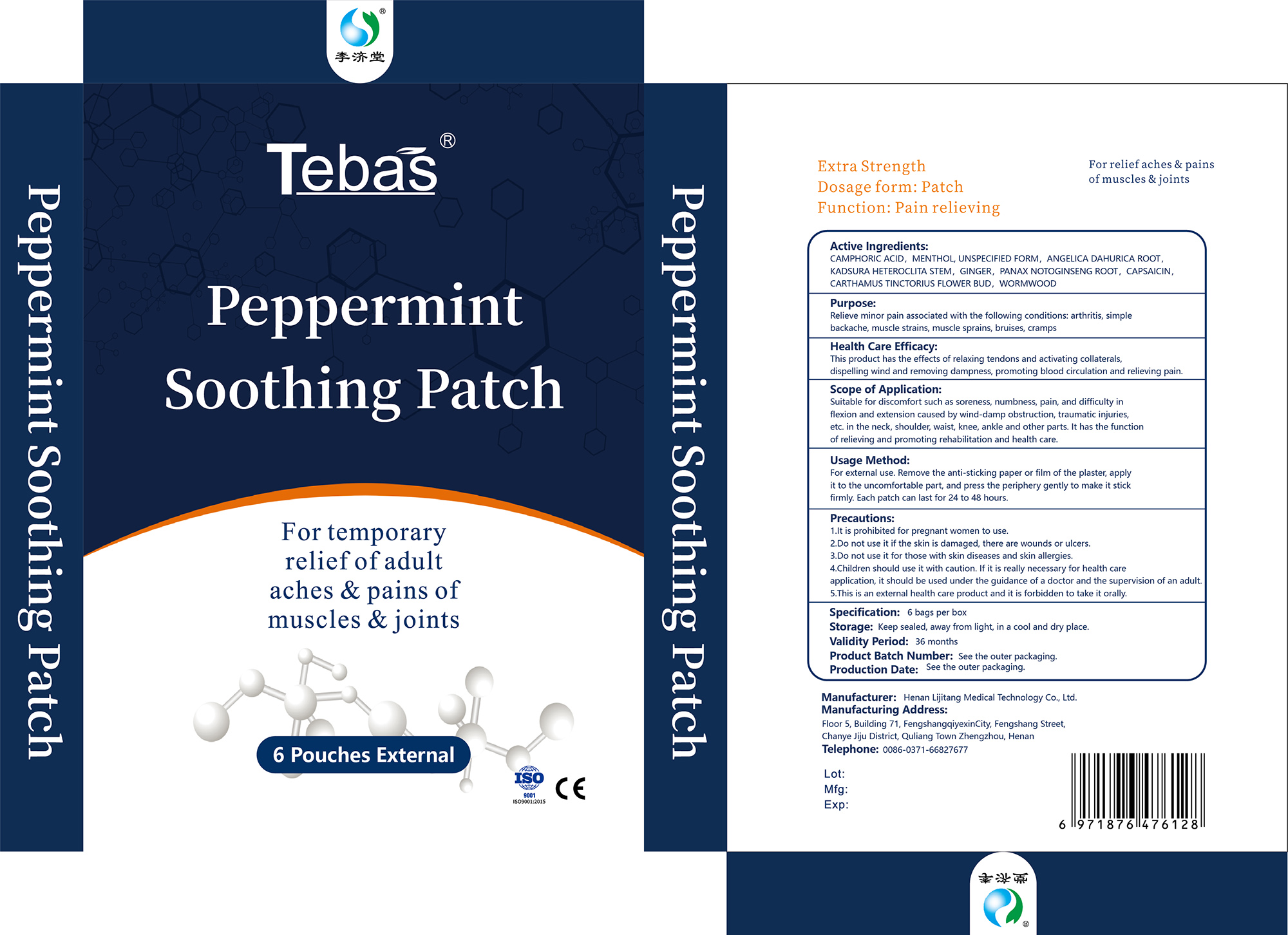 DRUG LABEL: Peppermint Soothing Patch
NDC: 85305-002 | Form: PATCH
Manufacturer: Henan Lijitang Medical Technology Co., Ltd.
Category: otc | Type: HUMAN OTC DRUG LABEL
Date: 20250313

ACTIVE INGREDIENTS: MENTHOL, UNSPECIFIED FORM 0.05 g/1 1; CAMPHORIC ACID 0.035 g/1 1
INACTIVE INGREDIENTS: CARTHAMUS TINCTORIUS FLOWER BUD; ANGELICA DAHURICA ROOT; WORMWOOD; PANAX NOTOGINSENG ROOT; KADSURA COCCINEA ROOT; CAPSAICIN; GINGER

Peppermint Soothing Patch

ACTIVE INGREDIENT

CAMPHORIC ACID 3.5%
MENTHOL, UNSPECIFIED FORM 5%

PURPOSE

Relieve minor pain associated with the following conditions: arthritis, simplebackache,muscle strains, muscle sprains, bruises, cramps

WARNINGS

For external use only

DO NOT USE

1.lt is prohibited for pregnant women to use.
2.Do not use it if the skin is damaged, there are wounds or ulcers.
3.Do not use it for those with skin diseases and skin allergies.
4.Children should use it with caution. lf it is really necessary for health careapplication, it should be used under the guidance of a doctor and the supervision of an adult.
5.This is an external health care product and it is forbidden to take it orally.

WHEN USING

Suitable for discomfort such as soreness, numbness, pain, and difficulty inflexion and extension caused by wind-damp obstruction, traumatic injuries,etc. in the neck, shoulder, waist, knee, ankle and other parts. lt has the functionof relieving and promoting rehabilitation and health care.

KEEP OUT OF REACH OF CHILDREN

4.Children should use it with caution. lf it is really necessary for health careapplication, it should be used under the guidance of a doctor and the supervision of an adult.

DOSAGE AND ADMINISTRATION

For external use. Remove the anti-sticking paper or film of the plaster, applyit to the uncomfortable part, and press the periphery gently to make it stickfirmly. Each patch can last for 24 to 48 hours.

INACTIVE INGREDIENT

ANGELICA DAHURICA ROOT
KADSURA HETEROCLITA STEM
GINGER
PANAX NOTOGINSENG ROOT
CARTHAMUS TINCTORIUS FLOWER BUD
CAPSAICIN
WORMWOOD

INDICATIONS AND USAGE

Relieve minor pain associated with the following conditions: arthritis, simplebackache, muscle strains, muscle sprains, bruises, cramps